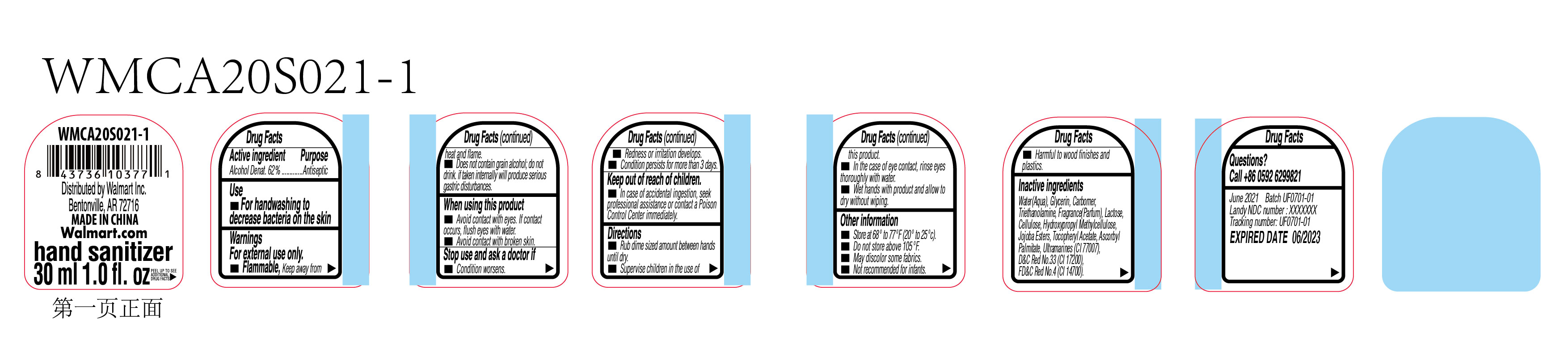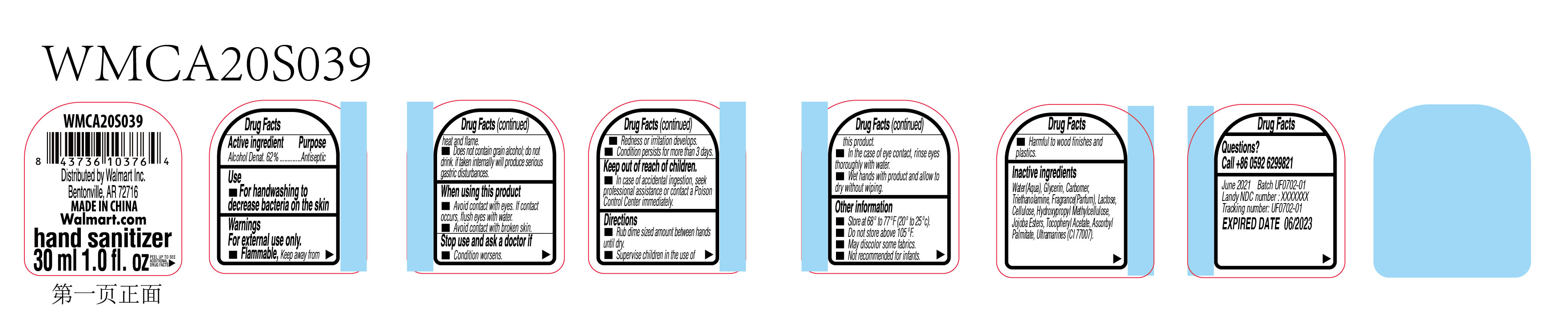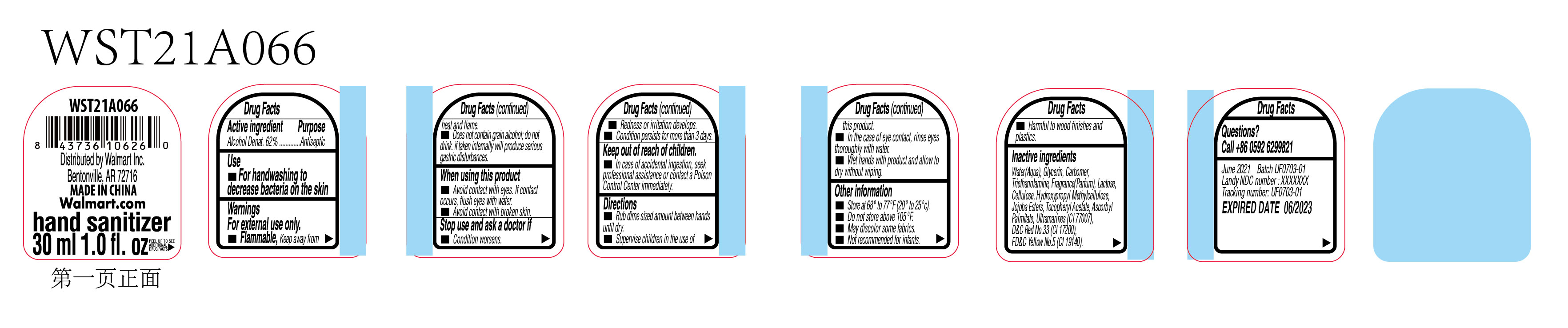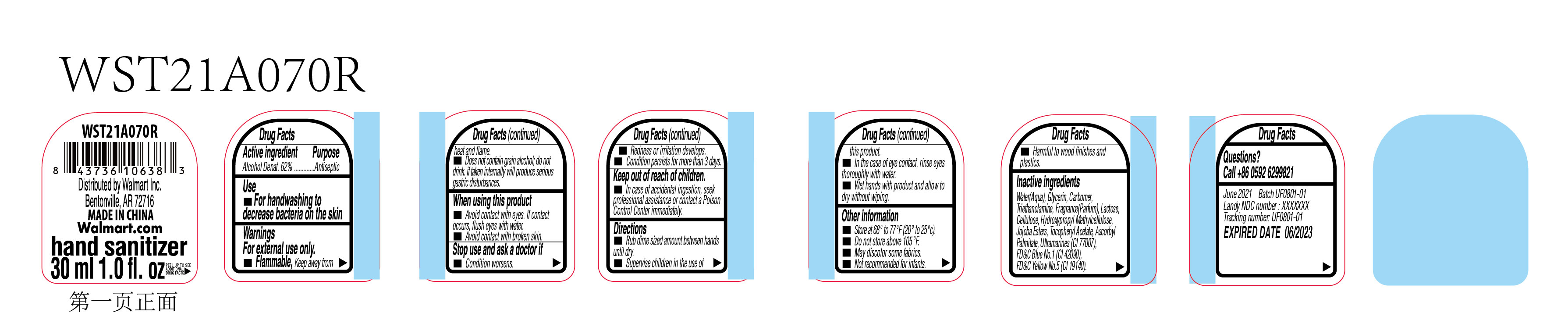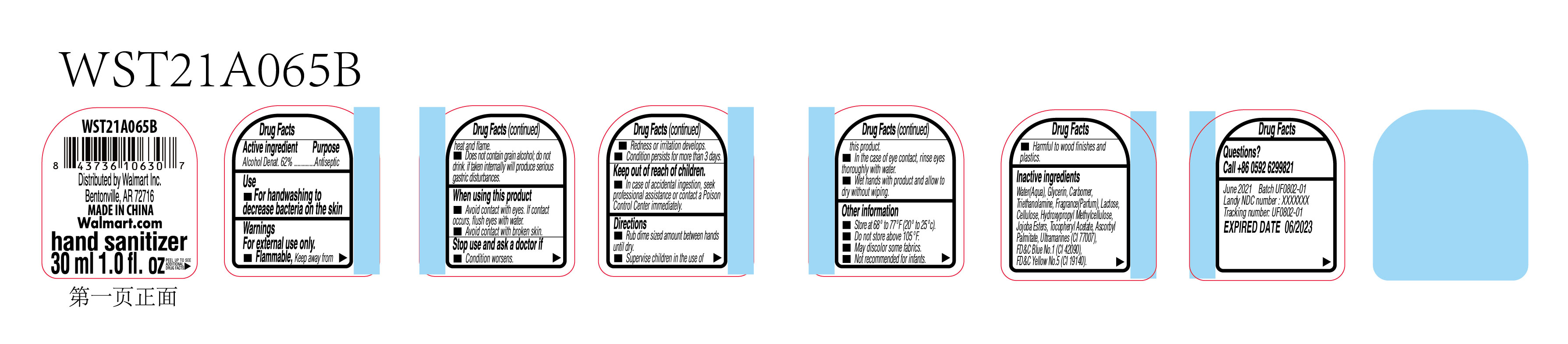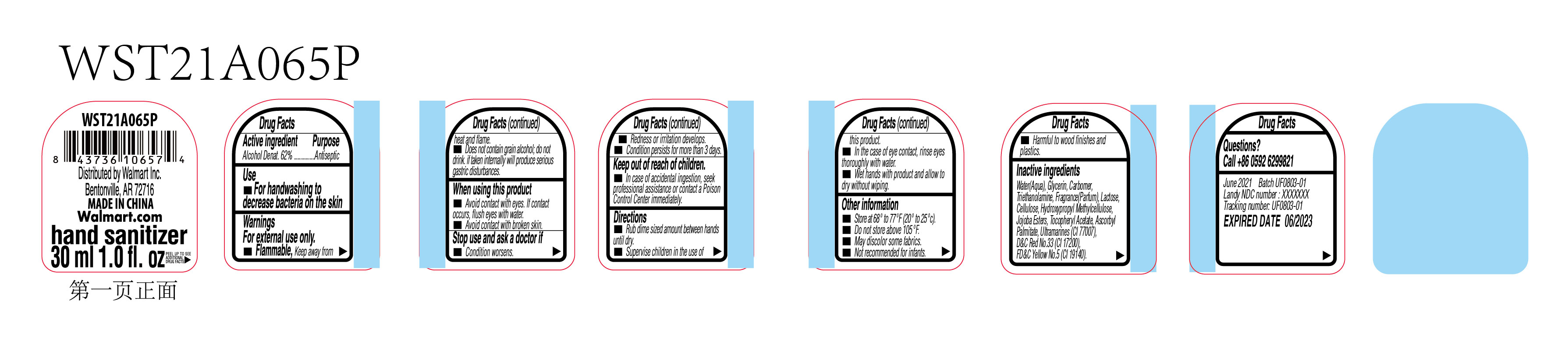 DRUG LABEL: Hand Sanitizer
NDC: 51706-964 | Form: GEL
Manufacturer: Landy International
Category: otc | Type: HUMAN OTC DRUG LABEL
Date: 20210518

ACTIVE INGREDIENTS: ALCOHOL 62 mL/100 mL
INACTIVE INGREDIENTS: GLYCERIN; TROLAMINE; WATER; POWDERED CELLULOSE; ALPHA-TOCOPHEROL ACETATE; ASCORBYL PALMITATE; CARBOMER HOMOPOLYMER, UNSPECIFIED TYPE; LACTOSE, UNSPECIFIED FORM; HYPROMELLOSES; JOJOBA OIL, RANDOMIZED

Active Ingredient(s)

Alcohol denat 62%

Purpose

Antiseptic

Use

for hadwashing to decrease bacteria on the skin

Warnings

For external use only. Flammable. Keep away from heat or flame

Do not use

dose not contain grain alcohol,do not drink,if taken internally will produce serious gastric distubances.

When using this product

avoid contact with eyes,if contact occurs,flush eyes with water

avoid contact with broken skin

Stop use and ask a doctor if condition worsens

redness or irrtation develops

contidion persists fro more than 3 days

Keep out of reach of children.

in case of accidental ingestion ,seek professinal assistance or contact a Poison Control Center immediately.

Directions

- rub dime sized amount between hands until dry.
- supervise children in the use of this product.
- in the case of eye contact ,rinse eyes thoroughly with water.
- wet hands with product and allow to dry without wiping.

Other information

Store at 68° to 77F(20° to 25°c).
Do not store above 105°.
May discolor some fabrics.
Not recommended for infants.
Harmful to wood finishes and
plastics.

Inactive ingredients

Water(Aqua), Glycerin, Carbome,Triethanolamine, Fragrance(Parfum),Lactose,
Cellulose, Hydroxypropyl Methylcellulose,Jojoba Estes, locopheryl Acetate, Ascorbyl,Palmitate, Ultramarines(CI 77007),
D&C Red NO.33(CI 17200),FD&C YVellow No.5(Cl 19140).

Package Label - Principal Display Panel

30 mL WMCA20S021-1 NDC: 51706-964-01

30 mL WMCA20S039 NDC: 51706-964-02

30 mL WST21A066 NDC: 51706-964-03

30 mL WST21A070R NDC: 51706-964-04

30 mL WST21A065B NDC: 51706-964-05

30 mL WST21A065P NDC: 51706-964-06